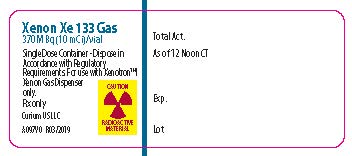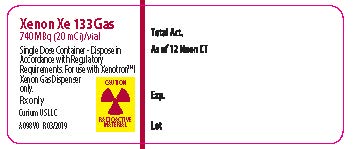 DRUG LABEL: Xenon, Xe-133
NDC: 69945-097 | Form: GAS
Manufacturer: Curium US LLC
Category: prescription | Type: HUMAN PRESCRIPTION DRUG LABEL
Date: 20241016

ACTIVE INGREDIENTS: XENON XE-133 5 mCi/1 mL
INACTIVE INGREDIENTS: AIR

Xenon Xe 133 Gas
Rx only
Diagnostic

DESCRIPTION

Xenon Xe 133 Gas is for diagnostic inhalation use only. It is supplied in vials containing either 370 or 740 megabecquerels (10 or 20 millicuries) of Xenon Xe 133 Gas in 2 milliliters of carrier xenon and atmospheric air.

Xenon Xe 133 Gas is chemically and physiologically similar to elemental xenon, a non-radioactive gas which is physiologically inert except for anesthetic properties at high doses.

Xenon Xe 133 is produced by fission of Uranium U 235. At the time of calibration, it contains no more than 0.3% Xenon Xe 133m, no more than 1.5% Xenon Xe 131m, no more than 0.06% Krypton Kr 85 and no more than 0.01% Iodine I 131, with no less than 99.9% total radioactivity as radioxenon. Table 1 shows the effect of time on radionuclidic composition.

Table 1. Radionuclidic Composition

Percent of Total Radioactivity
Days | % Xe-133 | % Xe-133m | % Xe-131m | % Kr-85 | % I-131
-5 | >98.3 | <0.6 | <1.0 | <0.03 | <0.01
0 [Calibration Date] | >98.1 | <0.3 | <1.5 | <0.06 | <0.01
7 | >97.2 | <0.08 | <2.5 | <0.15 | <0.02
14 [Expiration Date] | >95.7 | <0.02 | <4.1 | <0.37 | <0.02

PHYSICAL CHARACTERISTICS

Xenon Xe 133 decays by beta and gamma emissions with a physical half-life of 5.245 days. [Kocher, David C., "Radioactive Decay Data Tables," DOE/TIC-11026, 138 (1981).] Photons that are useful for detection and imaging studies as well as the principal beta emission are listed in Table 2.

Table 2. Principal Radiation Emission Data

Radiation | Mean % Per; Disintegration | Energy; (keV)
Beta-2 | 99.3 | 100.6 Avg.
Gamma-2 | 36.5 | 81.0
K alpha x-rays | 38.9 | 30.8 Avg.
K beta x-rays | 9.1 | 35.0 Avg.

EXTERNAL RADIATION

The specific gamma ray constant for Xenon Xe 133 is 0.51 R/hr-mCi at 1 cm. The first half-value thickness is 0.0035 cm of Pb.

A range of values for the relative attenuation of the radiation emitted by this radionuclide that results from interposition of various thicknesses of Pb is shown in Table 3. For example, the use of 0.2 cm of Pb will decrease the external radiation exposure by a factor of about 1000.

Table 3. Radiation Attenuation by Lead Shielding

Shield; Thickness (Pb), cm | Coefficient; of Attenuation
0.0035 | 0.5
0.037 | 10^-1
0.12 | 10^-2
0.20 | 10^-3
0.29 | 10^-4

To correct for physical decay of this radionuclide, the fractions that remain at selected time intervals after the date of calibration are shown in Table 4.

Table 4. Physical Decay Chart; Xenon Xe 133, Half-life 5.245 Days

Days | Fraction; Remaining | Days | Fraction; Remaining
0 [Calibration Day] | 1.000 | 8 | 0.347
1 | 0.876 | 9 | 0.304
2 | 0.768 | 10 | 0.267
3 | 0.673 | 11 | 0.234
4 | 0.589 | 12 | 0.205
5 | 0.516 | 13 | 0.179
6 | 0.453 | 14 | 0.157
7 | 0.397

CLINICAL PHARMACOLOGY

Xenon Xe 133 is a readily diffusible gas which is neither utilized nor produced by the body. It passes through cell membranes, freely exchanges between blood and tissue, and tends to concentrate more in body fat than in blood, plasma, water or protein solutions. In the concentrations recommended for diagnostic studies, it is physiologically inactive. Inhaled Xenon Xe 133 Gas will enter the alveolar wall and the pulmonary venous circulation via capillaries. Most of the Xenon Xe 133 Gas that enters the circulation from a single breath is returned to the lungs and exhaled after a single pass through the peripheral circulation.

INDICATIONS AND USAGE

Xenon Xe 133 Gas has been shown to be valuable for diagnostic inhalation studies for the evaluation of pulmonary function, for imaging the lungs and may also be applied to assessment of cerebral blood flow.

CONTRAINDICATIONS

None known.

WARNINGS

Xenon Xe 133 Gas delivery systems, i.e., respirators or spirometers, and associated tubing assemblies must be leakproof to avoid loss of radioactivity into the laboratory environs not specifically protected by exhaust systems.

Xenon Xe 133 Gas adheres to some plastics and rubber and should not be allowed to stand in tubing or respirator containers. Loss of radioactivity due to such adherence may render the study nondiagnostic.

PRECAUTIONS

General

Xenon Xe 133 Gas as well as other radioactive drugs, must be handled with care and appropriate safety measures should be used to minimize radiation exposure to clinical personnel. Also, care should be taken to minimize radiation exposure to the patients consistent with proper patient management.

Exhaled Xenon Xe 133 Gas should be controlled in a manner that is in compliance with the appropriate regulations of the government agency authorized to license the use of radionuclides.

Radiopharmaceuticals should be used only by physicians who are qualified by training and experience in the safe use and handling of radionuclides and whose experience and training have been approved by the appropriate government agency authorized to license the use of radionuclides.

Carcinogenesis, Mutagenesis, Impairment of Fertility

No long-term animal studies have been performed to evaluate carcinogenic potential, mutagenic potential or whether this drug affects fertility in males or females.

Pregnancy

Animal reproduction studies have not been conducted with Xenon Xe 133 Gas. It is also not known whether Xenon Xe 133 Gas can cause fetal harm when administered to a pregnant woman or can affect reproduction capacity. Xenon Xe 133 Gas should be given to a pregnant woman only if clearly needed.

Ideally, all examinations that use radiopharmaceuticals, especially those elective in nature, of a woman of childbearing capability should be performed during the first few (approximately 10) days following the onset of menses.

Nursing Mothers

It is not known whether this drug is excreted in human milk. Because many drugs are excreted in human milk, caution should be exercised when Xenon Xe 133 Gas is administered to a nursing woman.

Pediatric Use

Safety and effectiveness in pediatric patients have not been established.

ADVERSE REACTIONS

Adverse reactions specifically attributable to Xenon Xe 133 Gas have not been reported.

DOSAGE AND ADMINISTRATION

Xenon Xe 133 Gas is administered by inhalation from a closed respirator system or spirometer. The final patient dose should be measured by a suitable radioactivity calibration system immediately prior to administration.

The recommended activity range employed for inhalation by the average patient (70 kg) is:

Pulmonary function including imaging: 74 to 1110 megabecquerels (2 to 30 millicuries)

Cerebral blood flow: 370 to 1110 megabecquerels (10 to 30 millicuries)

This may be administered as a bolus into the tubing near the patient's mouthpiece or mask after the completion of a tidal exhalation, or by rebreathing for a period of approximately 5 minutes of the Xenon Xe 133 gas in equilibrium with the air contained in the closed system at concentrations of the radionuclide that may vary from 37 to 222 megabecquerels (1.0 to 6.0 millicuries) per liter.

RADIATION DOSIMETRY

The estimated absorbed radiation doses to an average patient (70 kg) for inhalation studies from a maximum dose of Xenon Xe 133 gas in 5, 7.5 and 10 liters are shown in Table 5. The values are the maximum absorbed dose that could be anticipated under the given conditions.

Table 5. Radiation Dose Estimates of Xenon Xe 133 [Atkins, Harold L., et al., Estimates of Radiation Absorbed Doses from Radioxenons in Lung Imaging. Task Group of the Medical Internal Radiation Dose Committee, Society of Nuclear Medicine, J. Nucl. Med., 21:459-465,1980.] : Absorbed Dose per 1110 megabecquerels (30 millicuries) of Xenon Xe 133 Gas Administered by Inhalation

Tissue | Spirometer Volume (liters)
Tissue | 5 |  |  | 7.5 |  |  | 10
Tissue | Absorbed Radiation Doses
Tissue | mGy | Rad | mGy |  | Rad | mGy |  | Rad
Lung | 3.3 | 0.33 | 2.46 |  | 0.246 | 1.95 |  | 0.195
Red Marrow | 0.45 | 0.045 | 0.36 |  | 0.036 | 0.27 |  | 0.027
Ovaries | 0.39 | 0.039 | 0.30 |  | 0.030 | 0.24 |  | 0.024
Testes | 0.36 | 0.036 | 0.27 |  | 0.027 | 0.21 |  | 0.021
Total Body | 0.42 | 0.042 | 0.33 |  | 0.033 | 0.27 |  | 0.027

DIRECTIONS FOR DISPENSING

Transfer the appropriate Xenon Xe 133 Gas dose from the Xenon Xe 133 Gas unit dose vial(s) to a breathing device or spirometer utilizing the Xenotron™ I Xenon Gas Dispenser. Follow the directions for use that are provided with the Xenotron™ I Xenon Gas Dispenser.

Xenon Xe 133 Gas should not be used after 14 days from the date of calibration stated on the label.

ACTIVITY MEASUREMENTS

Calibrate a suitable commercial ionization chamber dose calibrator according to the manufacturer's instructions for that particular instrument. An instrument that gives direct radioactivity readouts is recommended.

Use a National Institute of Standards and Technology (NIST) Xenon Xe 133 standard for the initial calibration. Also establish a secondary standard, such as Americium Am 241, at that time for subsequent routine use. Other suitable radionuclides may also be used. Determine the effective readout of the secondary standard compared to the Xenon Xe 133 standard over the range of activities expected for routine measurements. Determine the radioactivities of the dose for administration as follows:

1. Check the dose calibrator for proper response with the secondary standard.
2. Insert the Xenon Xe 133 Gas unit dose vial in the dose calibrator and measure the apparent radioactivity of the Xenon Xe 133.
3. Correct for decay as necessary.

The radioactivity determined by this method is within 25% of the true value. This degree of accuracy includes variations attributed to small differences in geometry and radiation attenuation between the NIST standard ampule and the Xenon Xe 133 Gas unit dose vial.

HOW SUPPLIED

Xenon Xe 133 Gas is available in 2 milliliter vials with color-coded labels in 370 megabecquerel (10 millicurie; Catalog No. 097) and 740 megabecquerel (20 millicurie; Catalog No. 098) sizes. Both sizes are available in packages of 1, 3 and 5 vials, each with individual lead shielding.

STORAGE

Xenon Xe 133 Gas should be stored at controlled room temperature 20° to 25°C (68° to 77°F). [See USP Controlled Room Temperature.]

The U.S. Nuclear Regulatory Commission has approved distribution of this radiopharmaceutical to persons licensed to use byproduct material listed in Sections 35.200 and to persons who hold an equivalent license issued by an Agreement State.

©2022 Curium US LLC. CuriumTMand the Curium logo are trademarks of a Curium company.

Curium US LLC
Maryland Heights, MO 63043 USA

A097I0

R07/2022

CURIUM™

PRINCIPAL DISPLAY PANEL - 10 mCi

XENON Xe 133 GAS

370 MBq (10 mCi)/vial

CAUTION RADIOACTIVE MATERIAL

Single Dose Container -Dispose in Accordance with Regulatory Requirements. For use with Xenotron™ I Xenon Gas Dispenser only.

Rx only

Curium US LLC

A097V0

R03/2019

PRINCIPAL DISPLAY PANEL - 20 mCi

XENON Xe 133 GAS

740 MBq (20 mCi)/vial

CAUTION RADIOACTIVE MATERIAL

Single Dose Container -Dispose in Accordance with Regulatory Requirements. For use with Xenotron™ I Xenon Gas Dispenser only.

Rx only

Curium US LLC

A098V0

R03/2019